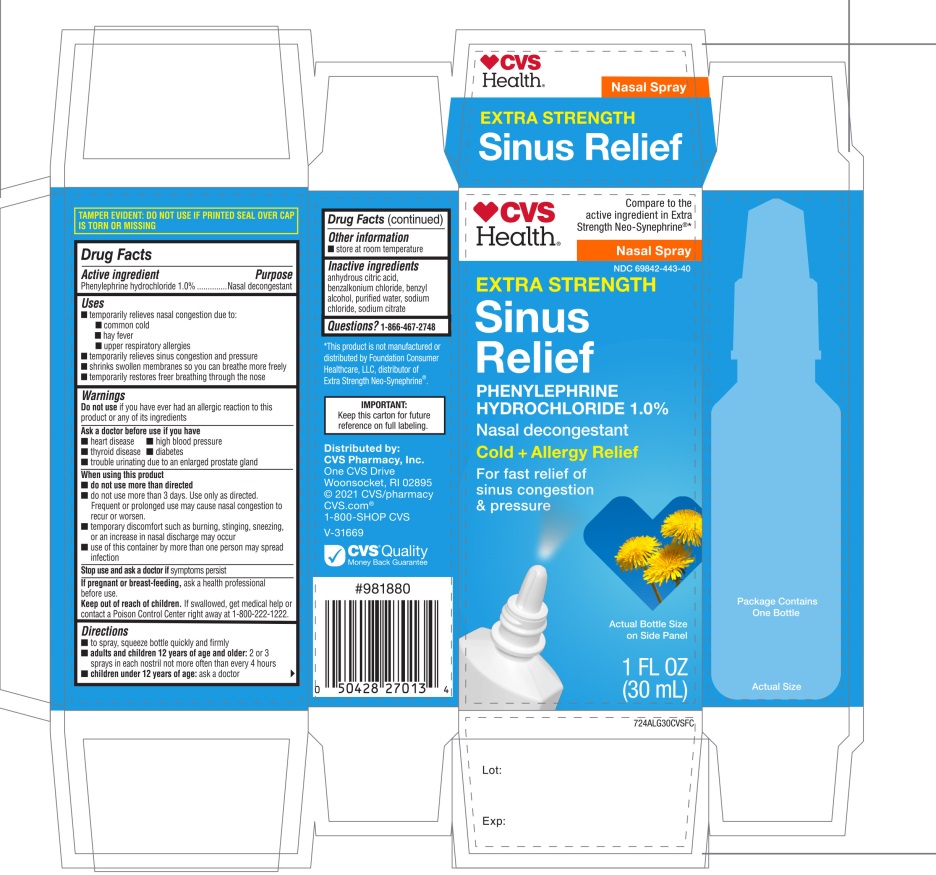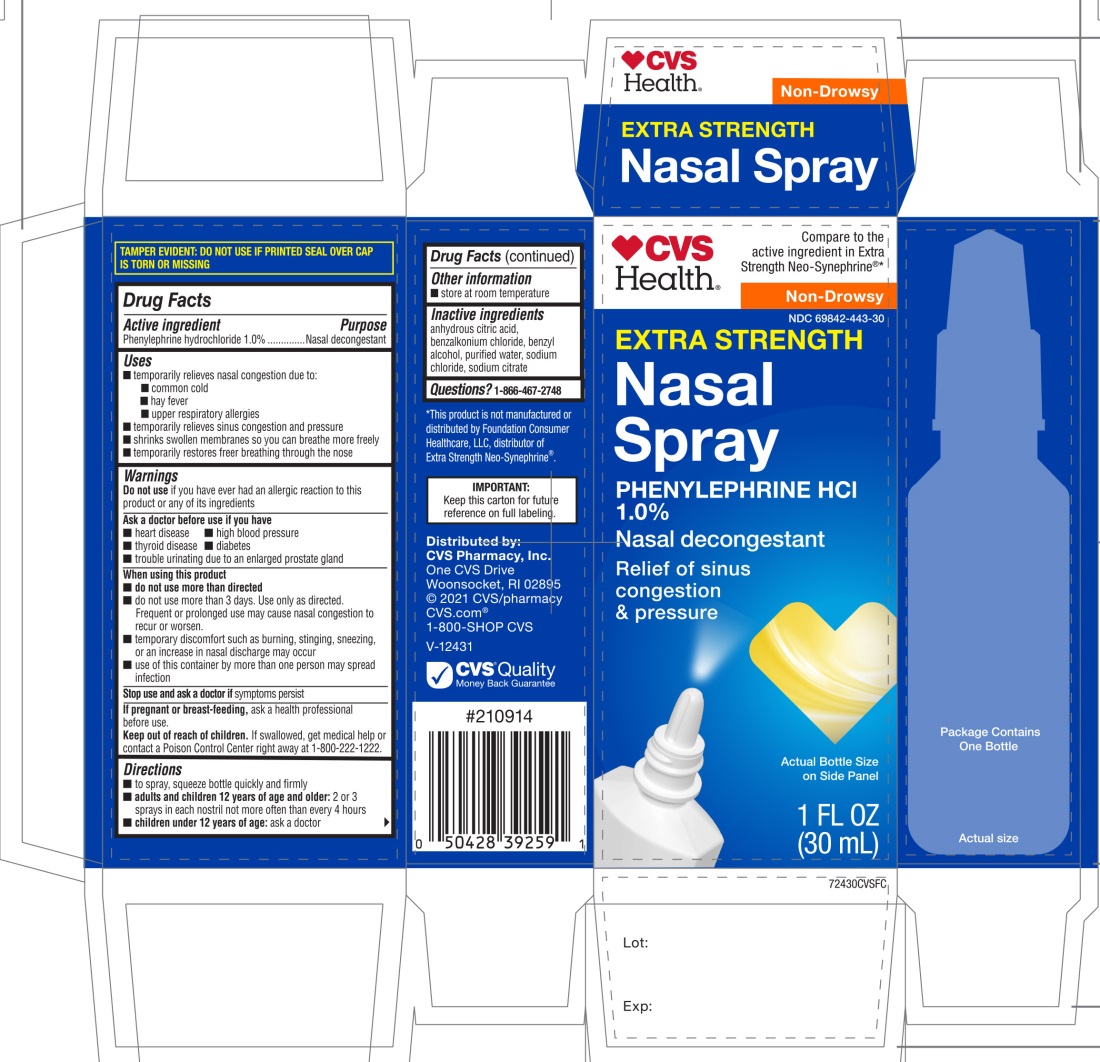 DRUG LABEL: Extra Strength Nasal
NDC: 69842-443 | Form: SPRAY
Manufacturer: CVS PHARMACY
Category: otc | Type: HUMAN OTC DRUG LABEL
Date: 20251209

ACTIVE INGREDIENTS: PHENYLEPHRINE HYDROCHLORIDE 1 g/100 mL
INACTIVE INGREDIENTS: ANHYDROUS CITRIC ACID; BENZALKONIUM CHLORIDE; BENZYL ALCOHOL; WATER; SODIUM CHLORIDE; SODIUM CITRATE, UNSPECIFIED FORM

Extra Strength Sinus Relief Phenylephrine Hydrochloride 1.0% Nasal Congestion 1 FL OZ

Active ingredients

Phenylephrine Hydrochloride 1.0 %

Purpose

Nasal decongestant

Uses

- temporarily relieves nasal congestion due to:
- common cold
- hay fever
- upper respiratory allergies (allergic rhinitis)
- temporarily relieves sinus congestion and pressure
- shrinks swollen membranes so you can breathe more freely
- temporarily restores freer breathing through the nose

Warnings

Do Not Use

If you have ever had an allergic reaction to this product or any of its ingredients

Ask a doctor before use if you have

- heart disease
- high blood pressure
- thyroid disease
- diabetes
- trouble urinating due to an enlarged prostate gland

When using this product

- do not use more than directed
- do not use for more than 3 days. Use only as directed.

Frequent or prolonged use may cause nasal congestion to recur or worsen

- temporary discomfort may occur such as burning, stinging, sneezing and increase in nasal discharge
- use of this container by more than one person may spread infection

Stop use and ask a doctor if

symptoms persist

If pregnant or breast-feeding

ask a health professional before use.

Keep out of reach of children.

If swallowed, get medical help or contact a Poison Control Center right away 1-800-222-1222

Directions

- to spray, squeeze bottle quickly and firmly
- adults and children 12 years older:2 or 3 sprays in each nostril not more often than every 4 hours.
- children under 12 years :ask a doctor

Other information

- store at room temperature

Inactive ingredients

anhydrous citric acid, benzalkonium chloride, benzyl alcohol, purified water, sodium chloride, sodium citrate

Questions

1-866-467-2748

Principal Display

Compare to the active ingredient in Extra Strength Neo-Synephrine®*

Extra Strength

Nasal Spray

Phenylephrine hydrochloride 1.0 %

Nasal Decongestant

NON-DROWSY

COLD+ALLERGY

Nasal Congestion RELIEF

You can use every 4 hours

Fast Relief Of:

Sinus Congestion & Pressure

- Colds, Allergies

*This product is not manufactured or distributed by Foundation Consumer Healthcare LLC, distributor of Extra Strength Neo-Synephrine®.

IMPORTANT: Keep this carton for future reference on full labeling.

Do not use if printed seal over cap is torn or missing

Distributed by:

CVS Pharmacy, Inc.

One CVS Drive

Woonsocket, RI 02895

© 2021 CVS/pharmacy, CVS.com®

1-800-SHOP CVS V-12431

CVS Quality Money Back guarantee

* This product is not manufactured or distributed by Foundation Consumer Healthcare LLC owner of the registered trademark Neo-Synephrine®Extra Strength.

Package Label for Extra Strength Nasal Spray